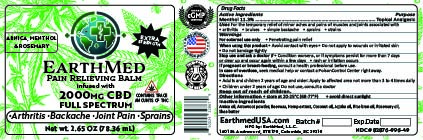 DRUG LABEL: Earthmed FS Pain relieving balm
NDC: 82876-996 | Form: SALVE
Manufacturer: Earthmed LLC
Category: otc | Type: HUMAN OTC DRUG LABEL
Date: 20250805

ACTIVE INGREDIENTS: MENTHOL 7.9 g/71.9 g
INACTIVE INGREDIENTS: .DELTA.9-TETRAHYDROCANNABINOLIC ACID 0.036 g/71.9 g; PEG-8 BEESWAX 19.02 g/71.9 g; JOJOBA OIL 5.1 g/71.9 g; COCONUT OIL 8.21 g/71.9 g; ROSEMARY OIL 0.59 g/71.9 g; RICE BRAN OIL 11.51 g/71.9 g; SHEA BUTTER 12.204 g/71.9 g; CANNABIDIOL 2.25 g/71.9 g; ARNICA MONTANA FLOWER WATER 4.22 g/71.9 g; MARANTA ARUNDINACEA ROOT 0.86 g/71.9 g

Earthmed FS pain relieving balm

Active Ingredients

Menthol...........11.3%

Purpose

Menthol 11.3%.........................Topical Analgesic

Purpose

Menthol 11.3%.........................Topical Analgesic

Uses

Temporary relief of aches and pains associated with arthritis, backache, joint pain, muscle strains, and sprains

Warnings

FOR EXTERNAL USE ONLY, provides penetrating pain relief

When using this product

Do not apply to wounds or irritated skin, and avoid contact with eyes

Stop use and ask a doctor if

The condition worsens, symptoms last more than 7 days, the condition clears but occurs again within a few days, Rash or irritation occurs

Stop use and ask a doctor if

Condition worsens, Symptoms last more than 7 days, Condition clears up but occurs again within a few days, Rash or irritations occurs

If pregnant or breastfeeding

Consult a health professional before use

In case of an overdose

seek medical help or contact a poison control center right away

Directions

Adults and children 12 years and over; apply to the affected area one to four times daily

Children 12 years and younger; ask a doctor

Keep out of reach of children

Keep out of reach of children

Other information

Store at 68-77 degrees F, Avoid direct sunlight

Inactive ingredients

Arnica Montana oil, Arrowroot powder, Beeswax, Full Spectrum Hemp Extract, Coconut oil, Rice bran oil, Rosemary oil, and Shea butter.